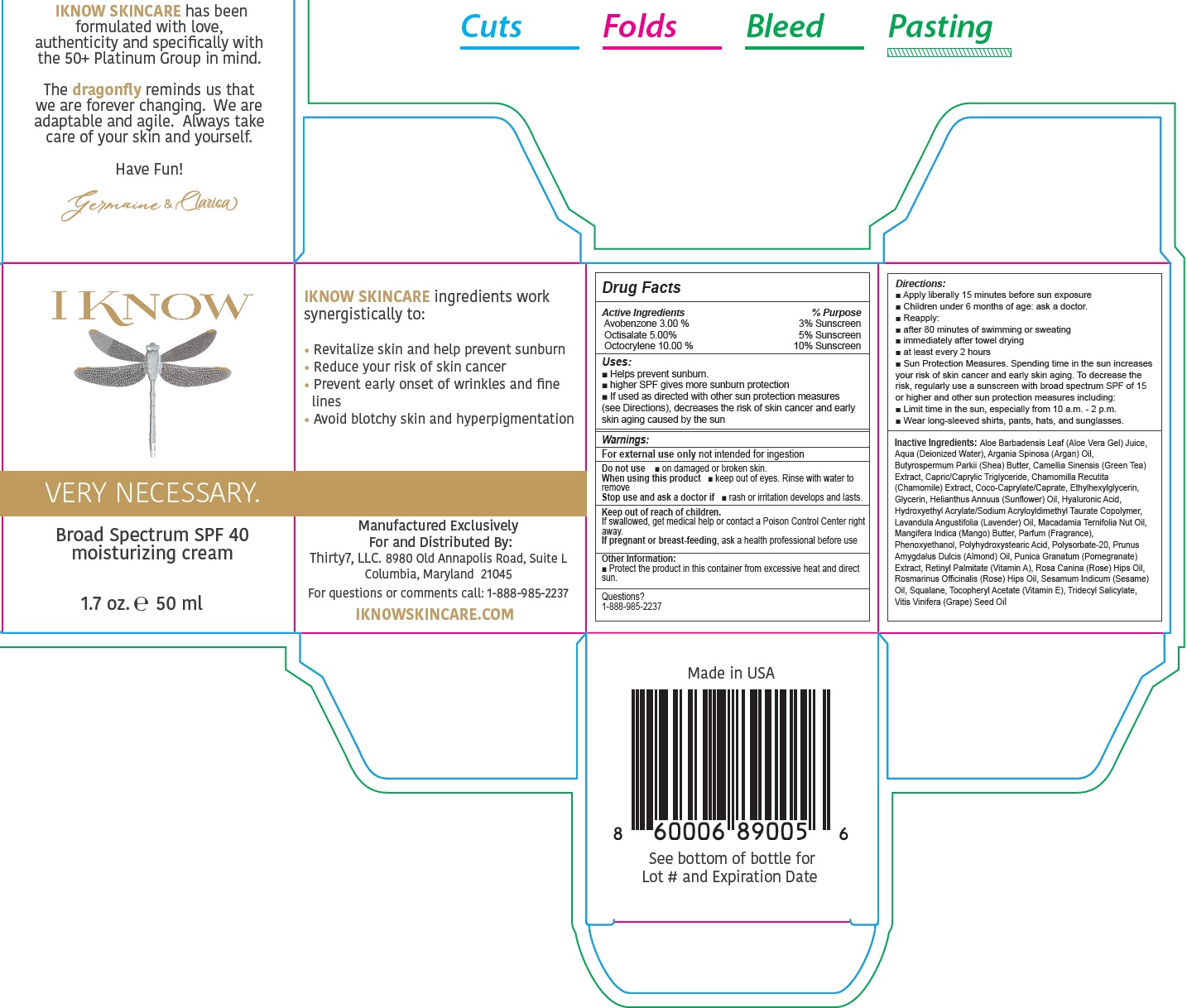 DRUG LABEL: I KNOW Very Necessary Broad Spectrum SPF-40 Moisturizing Cream
NDC: 82188-222 | Form: LOTION
Manufacturer: Thirty7 LLC
Category: otc | Type: HUMAN OTC DRUG LABEL
Date: 20231111

ACTIVE INGREDIENTS: AVOBENZONE 30 mg/1 mL; OCTISALATE 50 mg/1 mL; OCTOCRYLENE 100 mg/1 mL
INACTIVE INGREDIENTS: ALOE VERA LEAF; WATER; ARGAN OIL; SHEA BUTTER; GREEN TEA LEAF; TRICAPRILIN; CHAMOMILE; COCOYL CAPRYLOCAPRATE; ETHYLHEXYLGLYCERIN; GLYCERIN; HELIANTHUS ANNUUS FLOWERING TOP; HYALURONIC ACID; HYDROXYETHYL ACRYLATE/SODIUM ACRYLOYLDIMETHYL TAURATE COPOLYMER (100000 MPA.S AT 1.5%); LAVENDER OIL; MANGO; PHENOXYETHANOL; POLYSORBATE 20; ALMOND; PUNICA GRANATUM ROOT BARK; VITAMIN A PALMITATE; SESAME OIL UNSAPONIFIABLES; SQUALANE; .ALPHA.-TOCOPHEROL ACETATE; TRIDECYL SALICYLATE; GRAPE SEED OIL

I KNOW Very Necessary Broad Spectrum SPF-40 Moisturizing Cream

Active Ingredients

Avobenzone 3.00 % Octisalate 5.00% Octocrylene 10.00 %

Purpose

Sunscreen

Uses:

- Helps prevent sunburn.
- higher SPF gives more sunburn protection
- If used as directed with other sun protection measures (see Directions), decreases the risk of skin cancer and early skin aging caused by the sun

Warnings:

not intended for ingestion For external use only

Do not use

- on damaged or broken skin.

When using this product

- keep out of eyes. Rinse with water to remove

Stop use and ask a doctor if

- rash or irritation develops and lasts.

Keep out of reach of children.

If swallowed, get medical help or contact a Poison Control Center right away.

If pregnant or breast-feeding,

ask a health professional before use

Other Information:

- Protect the product in this container from excessive heat and direct sun.

Questions?

1-888-985-2237

Directions:

- Apply liberally 15 minutes before sun exposure
- Children under 6 months of age: ask a doctor.
- Reapply:
- after 80 minutes of swimming or sweating
- immediately after towel drying
- at least every 2 hours
- Sun Protection Measures. Spending time in the sun increases your risk of skin cancer and early skin aging. To decrease therisk, regularly use a sunscreen with broad spectrum SPF of 15 or higher and other sun protection measures including:
- Limit time in the sun, especially from 10 a.m. - 2 p.m.
- Wear long-sleeved shirts, pants, hats, and sunglasses.

Inactive Ingredients:

Aloe Barbadensis Leaf (Aloe Vera Gel) Juice, Aqua (Deionized Water), Argania Spinosa (Argan) Oil, Butyrospermum Parkii (Shea) Butter, Camellia Sinensis (Green Tea) Extract, Capric/Caprylic Triglyceride, Chamomilla Recutita (Chamomile) Extract, Coco-Caprylate/Caprate, Ethylhexylglycerin, Glycerin, Helianthus Annuus (Sunflower) Oil, Hyaluronic Acid, Hydroxyethyl Acrylate/Sodium Acryloyldimethyl Taurate Copolymer, Lavandula Angustifolia (Lavender) Oil, Macadamia Ternifolia Nut Oil, Mangifera Indica (Mango) Butter, Parfum (Fragrance), Phenoxyethanol, Polyhydroxystearic Acid, Polysorbate-20, Prunus Amygdalus Dulcis (Almond) Oil, Punica Granatum (Pomegranate) Extract, Retinyl Palmitate (Vitamin A), Rosa Canina (Rose) Hips Oil, Rosmarinus Officinalis (Rose) Hips Oil, Sesamum Indicum (Sesame) Oil, Squalane, Tocopheryl Acetate (Vitamin E), Tridecyl Salicylate, Vitis Vinifera (Grape) Seed Oil